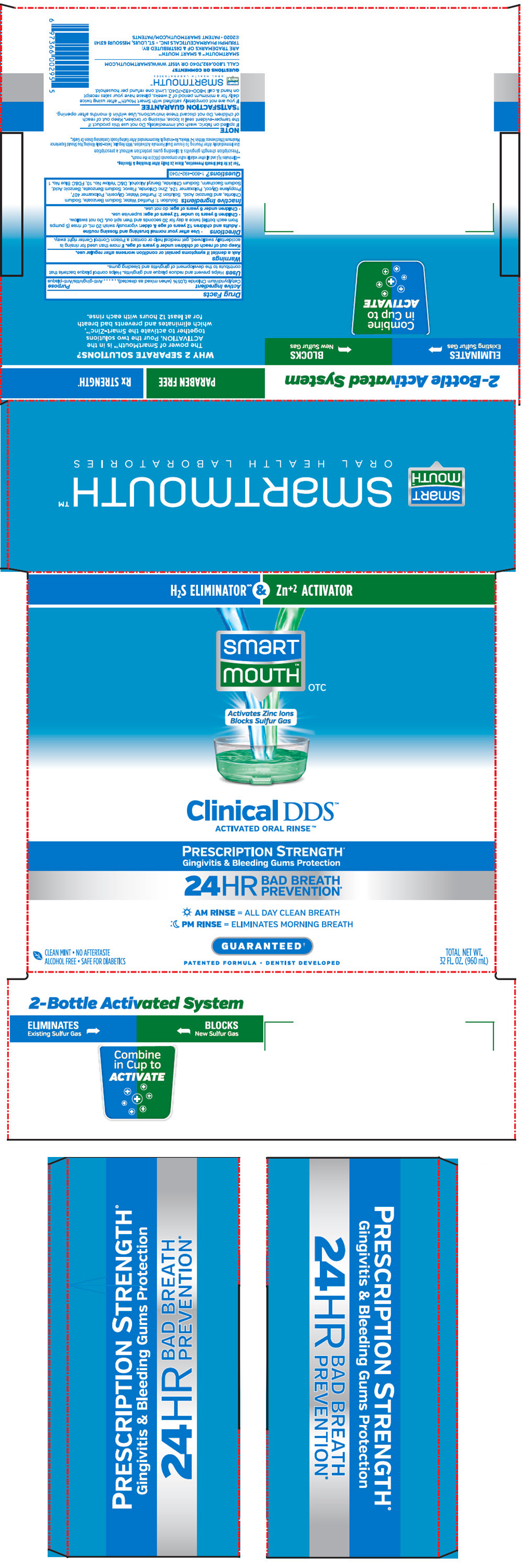 DRUG LABEL: SmartMouth Mouthwash 
NDC: 76357-285 | Form: KIT | Route: DENTAL
Manufacturer: Triumph Pharmaceuticals Inc.
Category: otc | Type: HUMAN OTC DRUG LABEL
Date: 20230207

ACTIVE INGREDIENTS: Cetylpyridinium Chloride 500 mg/20 mL
INACTIVE INGREDIENTS: Water; Glycerin; Poloxamer 407; Propylene Glycol; Poloxamer 124; Zinc Chloride; Sodium Benzoate; Benzoic Acid; Saccharin Sodium; Sodium Chloride; Benzyl Alcohol; D&C Yellow No. 10; FD&C Blue No. 1

SmartMouth™ Mouthwash
Clinical DDS™ Formula

DRUG FACTS

Active Ingredient

Cetylpyridinium Chloride 0.05% (when mixed as directed)

Purpose

Anti-gingivitis/Anti-plaque

Uses

Helps prevent and reduce plaque and gingivitis. Helps control plaque bacteria that contribute to the development of gingivitis and bleeding gums

Warnings

Ask a dentist if symptoms persist or condition worsens after regular use.

Keep out of reach of children under 6 years of age.

If more than used for rinsing is accidentally swallowed, get medical help or contact a Poison Control Center right away.

Directions

- Adults and children 12 years of age and older: vigorously swish 20 milliliters of rinse (5 pumps from each bottle) twice a day for 30 seconds and then spit out. Do not swallow.
- Children 6 years to under 12 years of age: supervise use.
- Children under 6 years of age: do not use.

Other information

- This rinse is not intended to replace brushing or flossing.

Inactive Ingredients

Solution 1: Purified Water, Sodium Benzoate, Sodium Chlorite, and Benzoic Acid

Solution 2: Purified Water, Glycerin, Poloxamer 407, Propylene Glycol, Poloxamer 124, Zinc Chloride, Flavor, Sodium Benzoate, Benzoic Acid, Sodium Saccharin, Sodium Chloride, Benzyl Alcohol, D&C Yellow No. 10, FD&C Blue No. 1

Questions or comments

1-800-492-7040

SMARTMOUTH™ & SMART MOUTH™
ARE TRADEMARKS OF & DISTRIBUTED BY:
TRIUMPH PHARMACEUTICALS INC. • ST. LOUIS, MISSOURI 63141

PRINCIPAL DISPLAY PANEL - Kit Cello Pack

H2S ELIMINATOR∞ & Zn^+2 ACTIVATOR

smart
mouth™
OTC

Activates Zinc Ions
Blocks Sulfur Gas

Clinical DDS™
ACTIVATED ORAL RINSE™

PRESCRIPTION STRENGTH^+
Gingivitis & Bleeding Gums Protection

24HR
BAD BREATH
PREVENTION*

AM RINSE = ALL DAY CLEAN BREATH
PM RINSE = ELIMINATES MORNING BREATH

GUARANTEED†

PATENTED FORMULA • DENTIST DEVELOPED

CLEAN MINT • NO AFTERTASTE
ALCOHOL FREE • SAFE FOR DIABETICS

TOTAL NET WT.
32 FL. OZ. (960 mL)